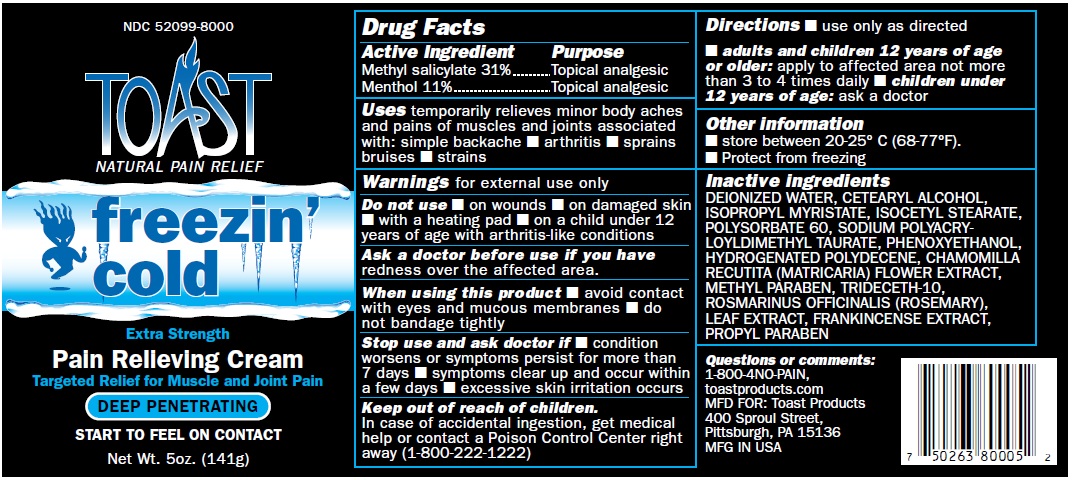 DRUG LABEL: FREEZIN COLD TOAST
NDC: 52099-8000 | Form: CREAM
Manufacturer: Q.A. Laboratories
Category: otc | Type: HUMAN OTC DRUG LABEL
Date: 20220117

ACTIVE INGREDIENTS: METHYL SALICYLATE 31 g/100 g; MENTHOL, UNSPECIFIED FORM 11 g/100 g
INACTIVE INGREDIENTS: WATER; CETOSTEARYL ALCOHOL; ISOPROPYL MYRISTATE; ISOCETYL STEARATE; POLYSORBATE 60; PHENOXYETHANOL; HYDROGENATED POLYDECENE TYPE I; MATRICARIA CHAMOMILLA WHOLE; METHYLPARABEN; TRIDECETH-10; FRANKINCENSE; ROSEMARY; PROPYLPARABEN

Drug Facts

Active Ingredient Purpose

Methyl salicylate 31% topical analgesic

Menthol 11% topical analgesic

PURPOSE

USES temporarily relieves minor body aches and pains of muscle and joints associated with: simple backache

arthritis sprains bruises strains

Warnings for external use only

Do not use ¡ on wounds ¡ on damaged skin
¡ with a heating pad ¡ on a child under 12
years of age with arthritis-like conditions

Ask a doctor before use if you have
redness over the affected area.

When using this product ¡ avoid contact
with eyes and mucous membranes ¡ do
not bandage tightly

Stop use and ask doctor if ■ condition
worsens or symptoms persist for more than
7 days ■ symptoms clear up and occur within
a few days ■ excessive skin irritation occurs

Keep out of reach of children.
In case of accidental ingestion, get medical
help or contact a Poison Control Center right
away (1-800-222-1222)

INDICATIONS AND USAGE

Directions ¡ use only as directed
¡ adults and children 12 years of age
or older: apply to af fected area not more
than 3 to 4 times daily ¡ children under
12 years of age: ask a doctor

Other information
■ store between 20-25° C (68-77°F).
■ Protect from freezing

DOSAGE AND ADMINISTRATION

apply to affected area not more
than 3 to 4 times daily

Inactive ingredients
DEIONIZED WATER, CETEARYL ALCOHOL,
ISOPROPYL MYRISTATE, ISOCETYL STEARATE,
POLYSORBATE 60, SODIUM POLYACRYLOYLDIMETHYL
TAURATE, PHENOXYETHANOL,
HYDROGENATED POLYDECENE, CHAMOMILLA
RECUTITA (MATRICARIA) FLOWER EXTRACT,
METHYL PARABEN, TRIDECETH-10,
ROSMARINUS OFFICINALIS (ROSEMARY),
LEAF EXTRACT, FRANKINCENSE EXTRACT,
PROPYL PARABEN

Questions or comments:
1-800-4NO-PAIN,
toastproducts.com
MFD FOR: Toast Products
400 Sproul Street,
Pittsburgh, PA 15136
MFG IN USA